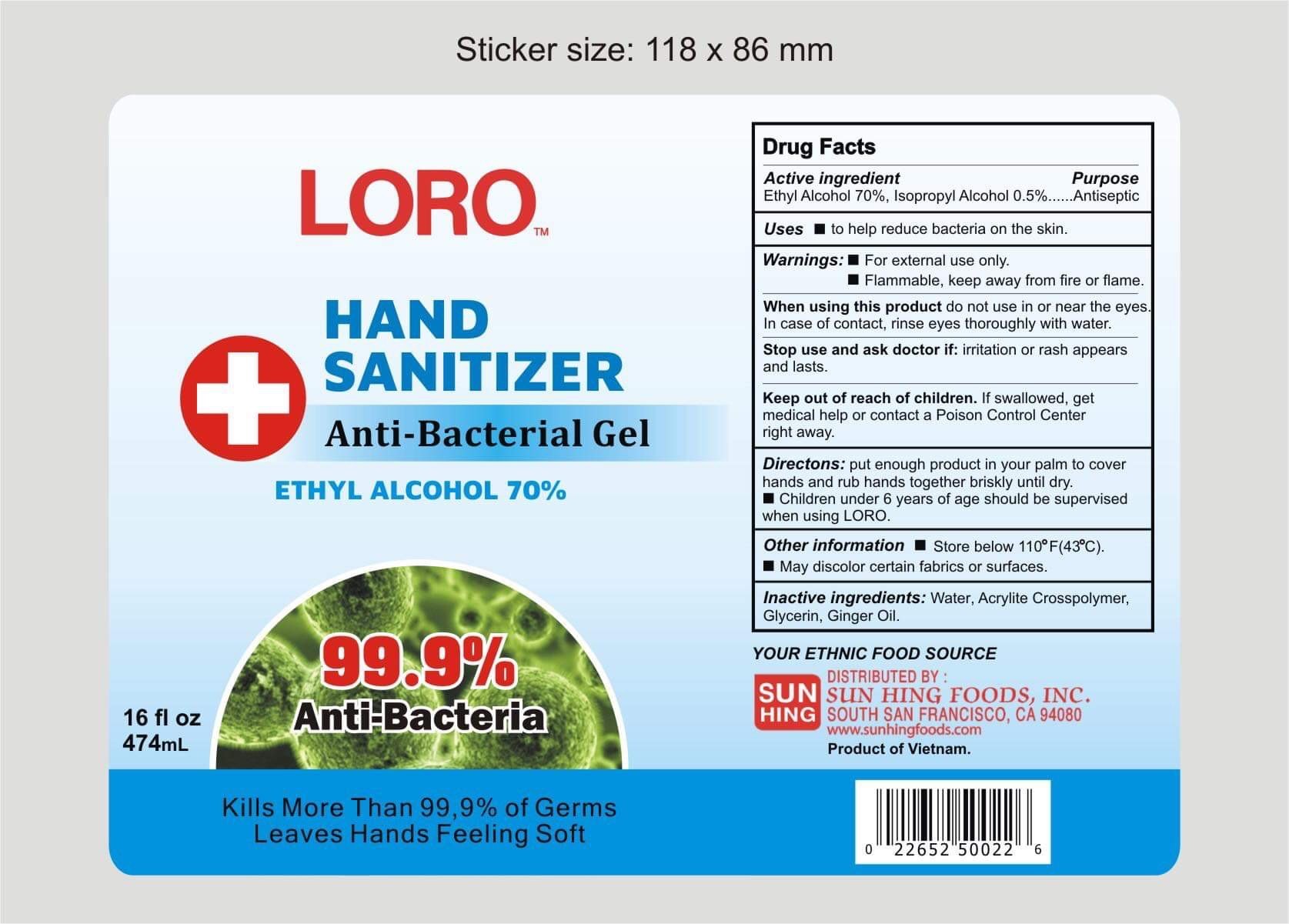 DRUG LABEL: Hand Sanitizer
NDC: 78185-000 | Form: GEL
Manufacturer: Sun Hing Foods Inc
Category: otc | Type: HUMAN OTC DRUG LABEL
Date: 20200615

ACTIVE INGREDIENTS: ISOPROPYL ALCOHOL 75 mL/100 mL
INACTIVE INGREDIENTS: GLYCERIN 1.45 mL/100 mL; WATER

LORO
HAND SANITIZER
Anti-Bacterial Spray
ETHYL ALCOHOL 70%

This is a hand sanitizer manufactured according to the Temporary Policy for Preparation of Certain Alcohol-Based Hand Sanitizer Products During the Public Health Emergency (CoViD-19); Guidance for Industry.

The hand sanitizer is manufactured using only the following United States Pharmacopoeia (USP) grade ingredients in the preparation of the product (percentage in final product formulation) consistent with World Health Organization (WHO) recommendations:

1. Isopropyl Alcohol (75%, v/v) in an aqueous solution denatured according to Alcohol and Tobacco Tax and Trade Bureau regulations in 27 CFR part 20.
2. Glycerol (1.45% v/v).
3. Hydrogen peroxide (0.125% v/v).
4. Sterile distilled water or boiled cold water.

The firm does not add other active or inactive ingredients. Different or additional ingredients may impact the quality and potency of the product.

Active Ingredient(s)

Ethyl Alcohol 70%, Isopropyl Alcohol 0.5%. Purpose: Antiseptic

Purpose

Antiseptic, Hand Sanitizer

Uses

To help reduce bacteria on the skin.

Warnings

For external use only. Flammable, Keep away from fire or flame

When using this product keep do not use in or near the eyes. In case of contact, rinse eyes thoroughly with water.
Stop use and ask a doctor if: irritation or rash appears and lasts.
Keep out of reach of children. If swallowed, get medical help or contact a Poison Control Center right away.

Stop use and ask a doctor if irritation or rash occurs. These may be signs of a serious condition.

Keep out of reach of children. If swallowed, get medical help or contact a Poison Control Center right away.

Directions

Directions: put enough product in your palm to cover hands and rub hands together briskly until dry.

* Children under 6 years of age should be supervised when using LORO.

Other information

- Store below 43C (110F)
- May discolor certain fabrics or surfaces

Manufacture by:

Hanoi Biology Chemistry Group Corporation

252/57 Tay Son, Trung Liet Ward, Dong Da District,

Hanoi, Vietnam

Tel: 024-66869828

Inactive ingredients

Water, Glycerin, Ginger Oil.

Package Label - Principal Display Panel

474 ml NDC: 78185-000-00